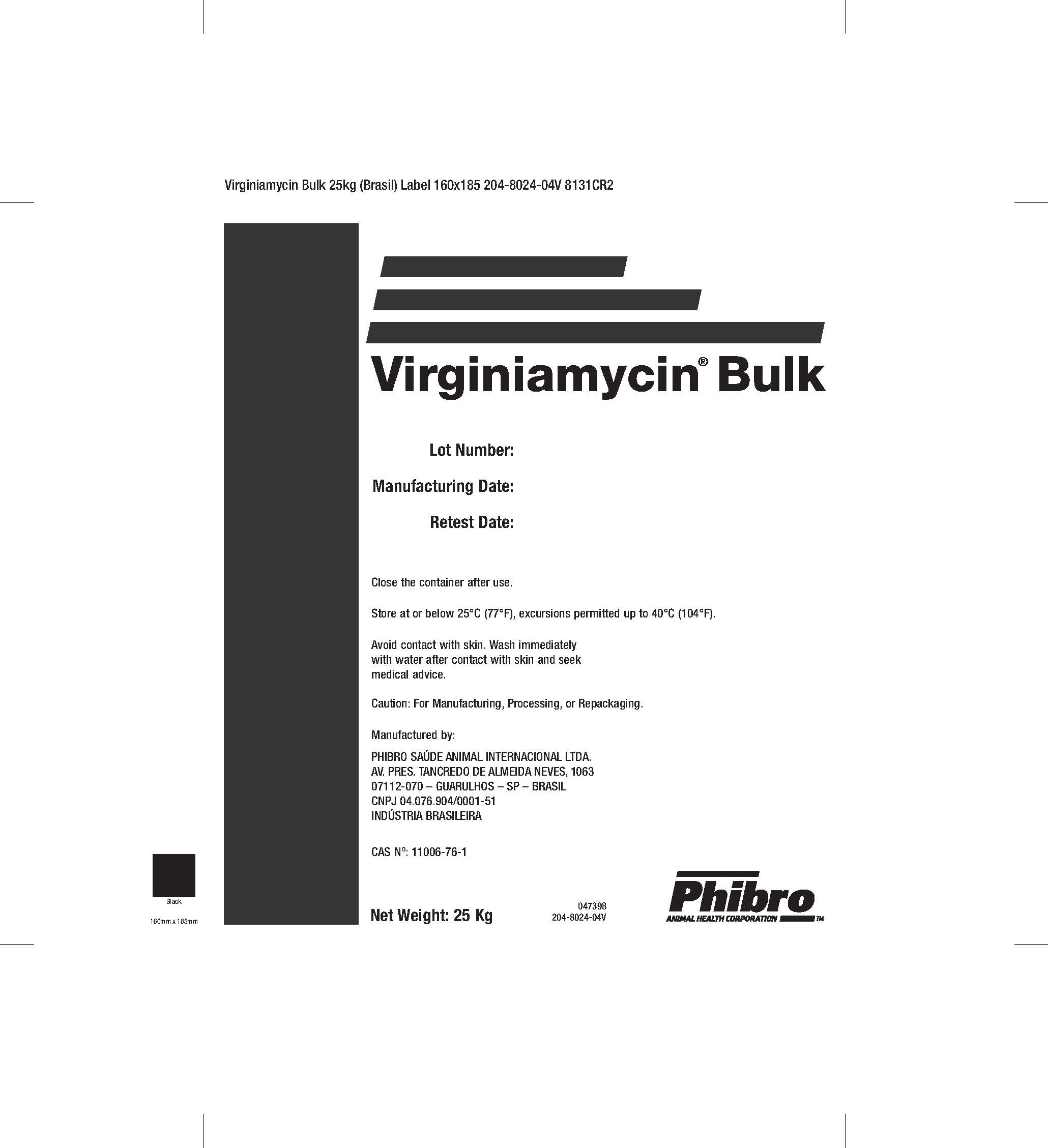 DRUG LABEL: Virginiamycin
NDC: 44476-3521 | Form: POWDER
Manufacturer: Phibro Saúde Animal Internacional Ltda.
Category: other | Type: BULK INGREDIENT - ANIMAL DRUG
Date: 20220603

ACTIVE INGREDIENTS: VIRGINIAMYCIN 100 kg/100 kg

Virginiamycin Bulk

VIRGINIAMYCIN BULK

Lot Number:

Manufacturing Date:

Retest Date:

Close container after use.

Store at or below 25°C (77°F), excursions permitted up to 40°C (104°F).

Avoid contact with skin. Wash immediately with water after contact with skin and seek medical advice.

Caution:

For Manufacturing, Processing and Repackaging.

Manufactured by:

PHIBRO SAUDE ANIMAL INTERNACIONAL LTDA.

AV. PRES. TANCREDO DE ALMEIDA NEVES, 1063

07112-070 - GUARULHOS - SP - BRASIL

CNPJ 04.076.904/0001-51

INDUSTRIAL BRASILEIRA

CAS N°.11006-76-1

NET WEIGHT 25KG047398 204-8024-04V

Add image transcription here...